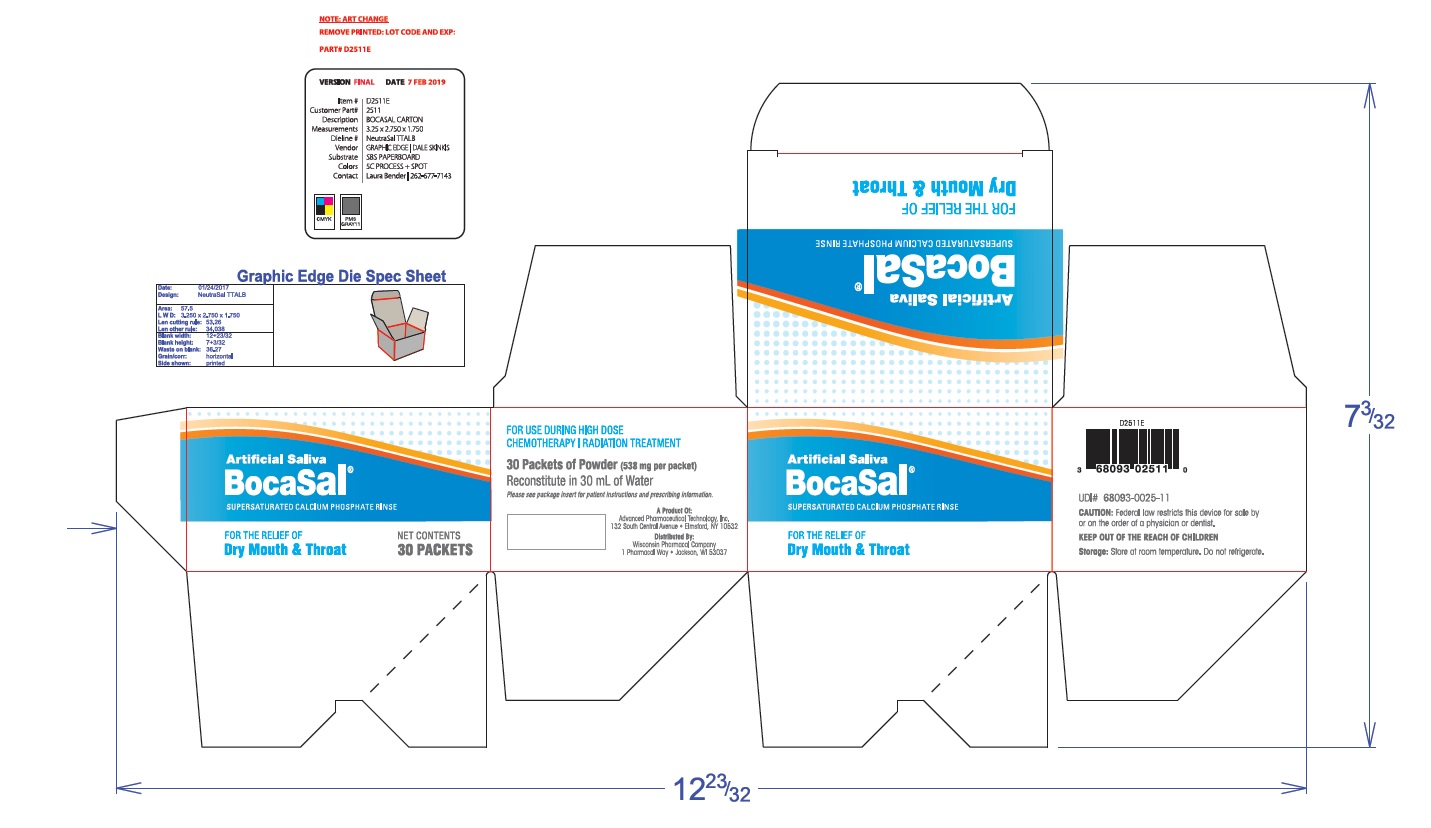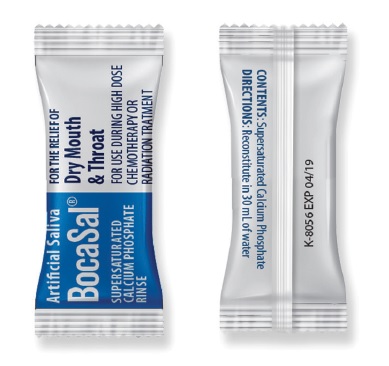 DRUG LABEL: BocaSal
NDC: 0368093
Manufacturer: Wisconsin Pharmacal Co., LLC
Category: other | Type: MEDICAL DEVICE
Date: 20190611

Medical Device